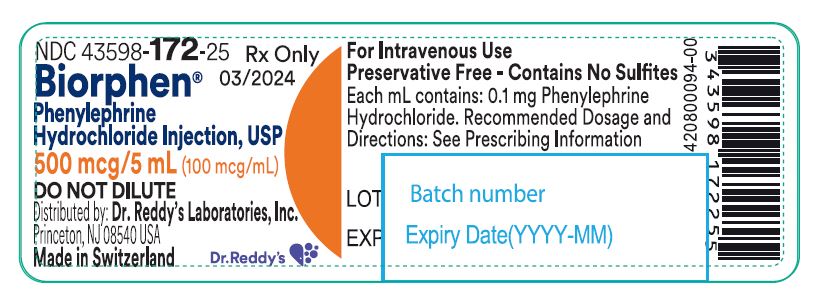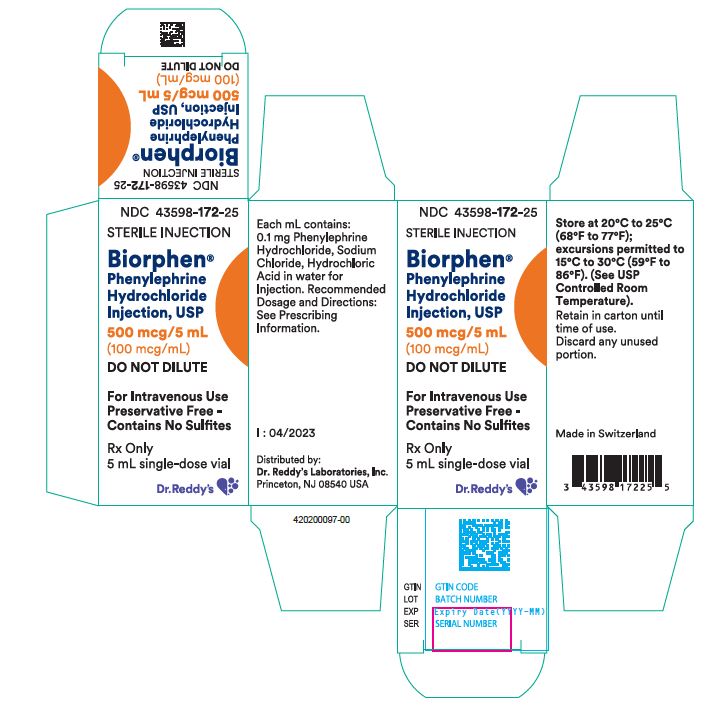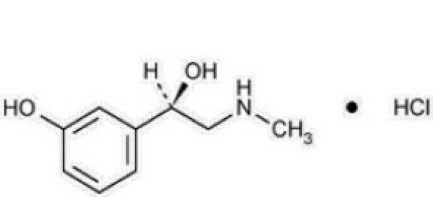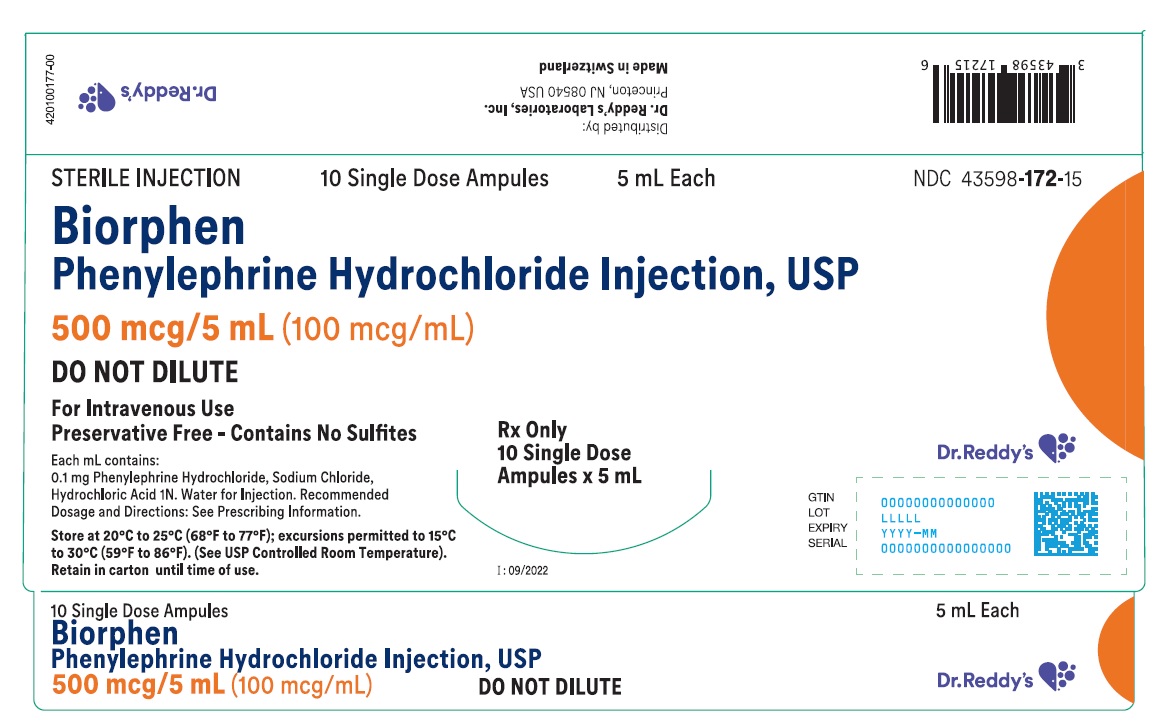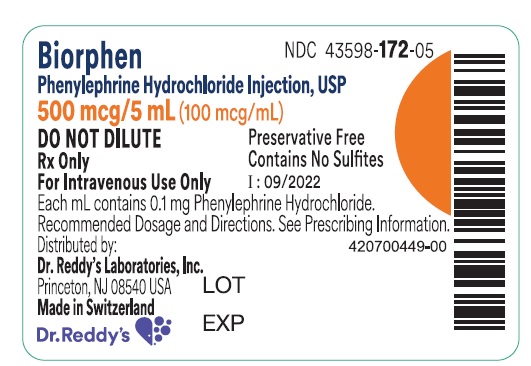 DRUG LABEL: Biorphen
NDC: 43598-172 | Form: INJECTION, SOLUTION
Manufacturer: Dr. Reddy's Laboratories Inc.
Category: prescription | Type: HUMAN PRESCRIPTION DRUG LABEL
Date: 20251223

ACTIVE INGREDIENTS: PHENYLEPHRINE HYDROCHLORIDE 0.1 mg/1 mL
INACTIVE INGREDIENTS: SODIUM CHLORIDE 9 mg/1 mL; HYDROCHLORIC ACID; WATER; NITROGEN

HIGHLIGHTS OF PRESCRIBING INFORMATION

These highlights do not include all the information needed to use BIORPHEN® safely and effectively. See full prescribing information for BIORPHEN.
BIORPHEN (phenylephrine hydrochloride) injection, for intravenous use
Initial U.S. Approval: 1954

1 INDICATIONS AND USAGE

BIORPHEN injection is an alpha-1 adrenergic receptor agonist indicated for the treatment of clinically important hypotension resulting primarily from vasodilation in the setting of anesthesia. (1)

2 DOSAGE AND ADMINISTRATION

- BIORPHEN 500 mcg/5 mL (100 mcg/mL)/mL injection MUST NOT BE DILUTED before administration as an intravenous bolus. It is supplied as a READY-TO-USE formulation. (2)
- BIORPHEN 10 mg/mL injection MUST BE DILUTED before administration as an intravenous bolus or continuous intravenous infusion to achieve the desired concentration. (2)

Dosing for treatment of hypotension during anesthesia

- Bolus intravenous injection: Initial dose is 40 mcg to 100 mcg. Additional boluses up to 200 mcg may be administered every
  1 to 2 minutes as needed. (2)
- Adjust the dose according to the pressor response (i.e., titrate to effect). (2)
- Biorphen 10 mg/mL Only: Continuous intravenous infusion:
  10 mcg/min to 35 mcg/min, titrating to effect, not to exceed 200 mcg/min. (2)

3 DOSAGE FORMS AND STRENGTHS

- Biorphen 500 mcg/5 mL (100 mcg/mL) Injection: Single-dose ampule containing 5 mL of solution for injection corresponding to 0.5 mg of phenylephrine hydrochloride per ampule. (3)
- Biorphen 500 mcg/5 mL (100 mcg/mL) Injection: Single-dose vial containing 5 mL of solution for injection corresponding to 0.5 mg of phenylephrine hydrochloride per vial.(3)
- Biorphen 10 mg/mL Injection: Single-dose ampule containing 1 mL of solution for injection corresponding to 10 mg of phenylephrine hydrochloride per ampule. (3)

4 CONTRAINDICATIONS

None (4)

5 WARNINGS AND PRECAUTIONS

Exacerbation of Angina, Heart Failure, or Pulmonary Arterial Hypertension: BIORPHEN can precipitate angina in patients with severe arteriosclerosis or history of angina, exacerbate underlying heart failure, and increase pulmonary arterial pressure. (5.1)
Peripheral and Visceral Ischemia: BIORPHEN can cause excessive peripheral and visceral vasoconstriction and ischemia to vital organs. (5.2)
Skin and Subcutaneous Necrosis: Extravasation during intravenous administration may cause necrosis or sloughing of tissue. (5.3)
Bradycardia: BIORPHEN can cause severe bradycardia and decreased cardiac output. (5.4)

6 ADVERSE REACTIONS

Most common adverse reactions during treatment: nausea, vomiting, and headache. (6)

To report SUSPECTED ADVERSE REACTIONS, contact Dr. Reddy's Laboratories Inc., at 1-888-375-3784 or FDA at 1-800-FDA-1088 or www.fda.gov/medwatch.

7 DRUG INTERACTIONS

Agonistic Effects (increase in BIORPHEN blood pressure effect) can occur with monoamine oxidase inhibitors (MAOI), oxytocin and oxytocic drugs, tricyclic antidepressants, angiotensin and aldosterone, atropine, steroids, norepinephrine transporter inhibitors, ergot alkaloids. (7.1)
Antagonistic Effects (decrease in BIORPHEN blood pressure effect) can occur with α-adrenergic antagonists, phosphodiesterase Type 5 inhibitors, mixed α- and β-receptor antagonists, calcium channel blockers, benzodiazepines and ACE inhibitors, centrally acting sympatholytic agents. (7.2)

FULL PRESCRIBING INFORMATION

1 INDICATIONS AND USAGE

BIORPHEN is indicated for the treatment of clinically important hypotension resulting primarily from vasodilation in the setting of anesthesia.

2 DOSAGE AND ADMINISTRATION

2.1 General Dosage and Administration Instructions

During BIORPHEN administration:

- Correct intravascular volume depletion.
- Correct acidosis. Acidosis may reduce the effectiveness of phenylephrine.

Parenteral drug products should be inspected visually for particulate matter and discoloration prior to administration. Do not use if the solution is colored or cloudy, or if it contains particulate matter. Discard any unused portion.

BIORPHEN 500 mcg/5 mL (100 mcg/mL) and 10 mg/mL Injection have important differences in administration instructions:

Administration Instructions for BIORPHEN 500 mcg/5 mL (100 mcg/mL) Injection:

BIORPHEN 500 mcg/5 mL (100 mcg/mL) injection MUST NOT BE DILUTED before administration as an intravenous bolus. It is supplied as READY-TO-USE formulation.

Administration Instructions for BIORPHEN 10 mg/mL Injection:
BIORPHEN 10 mg/mL injection MUST BE DILUTED before administration as an intravenous bolus or continuous intravenous infusion to achieve the desired concentration:
• Bolus: Dilute with normal saline or 5% dextrose in water.
• Continuous infusion: Dilute with normal saline or 5% dextrose in water.
The diluted solution should not be held for more than 4 hours at room temperature or for more than 24 hours under refrigerated conditions.

2.2 Dosing for Treatment of Hypotension during Anesthesia

The following are the recommended dosages for the treatment of hypotension during anesthesia.

BIORPHEN 500 mcg/5 mL (100 mcg/mL) Injection:

- The recommended initial dose is 40 mcg to 100 mcg administered by intravenous bolus. Additional boluses up to 200 mcg may be administered every 1 to 2 minutes as needed.
- Adjust dosage according to the blood pressure goal.

BIORPHEN 10 mg/mL Injection:
• The recommended initial dose is 40 mcg to 100 mcg administered by intravenous bolus. Additional boluses up to 200 mcg may be administered every 1 to 2 minutes as needed.
• If blood pressure is below the target goal, start a continuous intravenous infusion with an infusion rate of 10 mcg/minute to 35 mcg/minute; not to exceed 200 mcg/minute.
• Adjust dosage according to the blood pressure goal.

2.3 Preparation of a 100 mcg/mL Solution for Bolus Intravenous Administration from BIORPHEN 10 mg/mL Injection

For bolus intravenous administration, prepare a solution containing a final concentration of 100 mcg/mL of BIORPHEN 10 mg/mL Injection:
• Withdraw 10 mg i.e. 1 mL of BIORPHEN 10 mg/mL Injection and dilute with 99 mL of 5% Dextrose Injection, USP or 0.9% Sodium Chloride Injection, USP.
• Withdraw an appropriate dose from the 100 mcg/mL solution prior to bolus intravenous administration.

2.4 Preparation of Solution for Continuous Intravenous Administration from BIORPHEN 10 mg/mL Injection

For continuous intravenous infusion, prepare a solution containing a final concentration of 20 mcg/mL of BIORPHEN 10 mg/mL Injection in 5% Dextrose Injection, USP or 0.9% Sodium Chloride Injection, USP.
• Withdraw 10 mg i.e. 1 mL of BIORPHEN 10 mg/mL Injection and dilute with 500 mL of 5% Dextrose Injection, USP or 0.9% Sodium Chloride Injection, USP.

3 DOSAGE FORMS AND STRENGTHS

BIORPHEN 500 mcg/5 mL (100 mcg/mL) Injection:

Ampule

BIORPHEN injection, 500 mcg/5 mL (100 mcg/mL), for intravenous use, is a clear and colorless solution available in a type I one point cut clear colorless glass single-dose ampule containing 5 mL of solution for injection, corresponding to 0.5 mg of phenylephrine hydrochloride per ampule (equivalent to 0.41 mg of phenylephrine base).

Vial

BIORPHEN injection, 500 mcg/5 mL (100 mcg/mL), for intravenous use, is a clear and colorless solution available in a type I clear colorless glass single-dose vial containing 5 mL of solution for injection, corresponding to 0.5 mg of phenylephrine hydrochloride per vial (equivalent to 0.41 mg of phenylephrine base).

BIORPHEN 10 mg/mL Injection:

BIORPHEN injection, 10 mg/mL, for intravenous use, is a clear and colorless solution available in a type I one point cut clear colorless glass single-dose ampule containing 1 mL of solution for injection, corresponding to 10 mg of phenylephrine hydrochloride per ampule (equivalent to 8.2 mg of phenylephrine base).

4 CONTRAINDICATIONS

None.

5 WARNINGS AND PRECAUTIONS

5.1 Exacerbation of Angina, Heart Failure, or Pulmonary Arterial Hypertension

Because of its increasing blood pressure effects, BIORPHEN can precipitate angina in patients with severe arteriosclerosis or history of angina, exacerbate underlying heart failure, and increase pulmonary arterial pressure.

5.2 Peripheral and Visceral Ischemia

BIORPHEN can cause excessive peripheral and visceral vasoconstriction and ischemia to vital organs, particularly in patients with extensive peripheral vascular disease.

5.3 Skin and Subcutaneous Necrosis

Extravasation of BIORPHEN can cause necrosis or sloughing of tissue. Avoid extravasation by checking infusion site for free flow.

5.4 Bradycardia

BIORPHEN can cause severe bradycardia and decreased cardiac output.

5.5 Renal Toxicity

BIORPHEN can increase the need for renal replacement therapy in patients with septic shock. Monitor renal function.

5.6 Risk of Augmented Pressor Affect in Patients with Autonomic Dysfunction

The increasing blood pressure response to adrenergic drugs, including BIORPHEN, can be increased in patients with autonomic dysfunction, as may occur with spinal cord injuries.

5.7 Pressor Effect with Concomitant Oxytocic Drugs

Oxytocic drugs potentiate the increasing blood pressure effect of sympathomimetic pressor amines including BIORPHEN [see Drug Interactions (7.1)], with the potential for hemorrhagic stroke.

6 ADVERSE REACTIONS

Adverse reactions to BIORPHEN are primarily attributable to excessive pharmacologic activity. Adverse reactions reported in published clinical studies, observational trials, and case reports of BIORPHEN are listed below by body system. Because these reactions are reported voluntarily from a population of uncertain size, it is not always possible to estimate their frequency reliably or to establish a causal relationship to drug exposure.

Cardiac disorders: Reflex bradycardia, lowered cardiac output, ischemia, hypertension, arrhythmias

Gastrointestinal disorders: Epigastric pain, vomiting, nausea

Nervous system disorders: Headache, blurred vision, neck pain, tremors

Vascular disorders: Hypertensive crisis

Respiratory, Thoracic and Mediastinal Disorders: Dyspnea

Skin and subcutaneous tissue disorders: Pruritis

7 DRUG INTERACTIONS

7.1 Interactions that Augment the Pressor Effect

The increasing blood pressure effect of BIORPHEN is increased in patients receiving:

- Monoamine oxidase inhibitors (MAOI)
- Oxytocin and oxytocic drugs
- Tricyclic antidepressants
- Angiotensin, aldosterone
- Atropine
- Steroids, such as hydrocortisone
- Norepinephrine transporter inhibitors, such as atomoxetine
- Ergot alkaloids, such as methylergonovine maleate

7.2 Interactions that Antagonize the Pressor Effect

The increasing blood pressure effect of BIORPHEN is decreased in patients receiving:

- α-adrenergic antagonists
- Phosphodiesterase Type 5 inhibitors
- Mixed α- and β-receptor antagonists
- Calcium channel blockers, such as nifedipine
- Benzodiazepines
- ACE inhibitors
- Centrally acting sympatholytic agents, such as reserpine, guanfacine

8 USE IN SPECIFIC POPULATIONS

8.1 Pregnancy

Risk Summary

Data from randomized controlled trials and meta-analyses with phenylephrine hydrochloride injection use in pregnant women during caesarean section have not established a drug-associated risk of major birth defects and miscarriage. These studies have not identified an adverse effect on maternal outcomes or infant Apgar scores [see Data]. There are no data on the use of phenylephrine during the first or second trimester. In animal reproduction and development studies in normotensive animals, evidence of fetal malformations was noted when phenylephrine was administered during organogenesis via a 1-hour infusion at 1.2 times the human daily dose (HDD) of 10 mg/60 kg/day. Decreased pup weights were noted in offspring of pregnant rats treated with 2.9 times the HDD [See Data].

The estimated background risk of major birth defects and miscarriage for the indicated population is unknown. All pregnancies have a background risk of birth defect, loss, or other adverse outcomes. In the U.S. general population, the estimated background risk of major birth defects and miscarriage in clinically recognized pregnancies is 2-4% and 15-20%, respectively.

Clinical Considerations

Disease-Associated Maternal and/or Embryofetal Risk

Untreated hypotension associated with spinal anesthesia for cesarean section is associated with an increase in maternal nausea and vomiting. A sustained decrease in uterine blood flow due to maternal hypotension may result in fetal bradycardia and acidosis.

Data

Human Data

Published randomized controlled trials over several decades, which compared the use of phenylephrine injection to other similar agents in pregnant women during cesarean section, have not identified adverse maternal or infant outcomes. At recommended doses, phenylephrine does not appear to affect fetal heart rate or fetal heart variability to a significant degree.

There are no studies on the safety of phenylephrine injection exposure during the period of organogenesis, and therefore, it is not possible to draw any conclusions on the risk of birth defects following exposure to phenylephrine injection during pregnancy. In addition, there are no data on the risk of miscarriage following fetal exposure to phenylephrine injection.

Animal Data

No clear malformations or fetal toxicity were reported when normotensive pregnant rabbits were treated with phenylephrine via continuous intravenous infusion over 1 hour (0.5 mg/kg/day; approximately equivalent to a HDD based on body surface area) from Gestation Day 7 to 19. At this dose, which demonstrated no maternal toxicity, there was evidence of developmental delay (altered ossification of sternebra).

In a non-GLP dose range-finding study in normotensive pregnant rabbits, fetal lethality and cranial, paw, and limb malformations were noted following treatment with 1.2 mg/kg/day of phenylephrine via continuous intravenous infusion over 1 hour (2.3-times the HDD). This dose was clearly maternally toxic (increased mortality and significant body weight loss). An increase in the incidence of limb malformation (hyperextension of the forepaw) coincident with high fetal mortality was noted in a single litter at 0.6 mg/kg/day (1.2-times the HDD) in the absence of maternal toxicity.

No malformations or embryo-fetal toxicity were reported when normotensive pregnant rats were treated with up to 3 mg/kg/day phenylephrine via continuous intravenous infusion over 1 hour (2.9-times the HDD) from Gestation Day 6 to 17. This dose was associated with some maternal toxicity (decreased food consumption and body weights).

Decreased pup weights were reported in a pre- and postnatal development toxicity study in which normotensive pregnant rats were administered phenylephrine via continuous intravenous infusion over 1 hour (0.3, 1.0, or 3.0 mg/kg/day; 0.29, 1, or 2.9 times the HDD) from Gestation Day 6 through Lactation Day 21). No adverse effects on growth and development (learning and memory, sexual development, and fertility) were noted in the offspring of pregnant rats at any dose tested. Maternal toxicities (mortality late in gestation and during lactation period, decreased food consumption and body weight) occurred at 1 and 3 mg/kg/day of phenylephrine (equivalent to and 2.9 times the HDD, respectively).

8.2 Lactation

Risk Summary

There are no data on the presence of Phenylephrine Hydrochloride Injection or its metabolite in human or animal milk, the effects on the breastfed infant, or the effects on milk production. The developmental and health benefits of breastfeeding should be considered along with the mother’s clinical need for phenylephrine hydrochloride injection and any potential adverse effects on the breastfed infant from phenylephrine hydrochloride injection or from the underlying maternal condition.

8.4 Pediatric Use

Safety and effectiveness in pediatric patients have not been established.

8.5 Geriatric Use

Clinical studies of phenylephrine did not include sufficient numbers of subjects aged 65 and over to determine whether they respond differently from younger subjects. Other reported clinical experience has not identified differences in responses between the elderly and younger patients. In general, dose selection for an elderly patient should be cautious, usually starting at the low end of the dosing range, reflecting the greater frequency of decreased hepatic, renal, or cardiac function, and of concomitant disease or other drug therapy.

8.6 Hepatic Impairment

In patients with liver cirrhosis [Child Pugh Class B and Class C], dose-response data indicate decreased responsiveness to phenylephrine. Start dosing in the recommended dose range but more phenylephrine may be needed in this population.

8.7 Renal Impairment

In patients with end stage renal disease (ESRD), dose-response data indicate increased responsiveness to phenylephrine. Consider starting at the lower end of the recommended dose range, and adjusting dose based on the target blood pressure goal.

10 OVERDOSAGE

Overdose of BIORPHEN (phenylephrine hydrochloride) can cause a rapid rise in blood pressure. Symptoms of overdose include headache, vomiting, hypertension, reflex bradycardia, a sensation of fullness in the head, tingling of the extremities, and cardiac arrhythmias including ventricular extrasystoles and ventricular tachycardia.

11 DESCRIPTION

Phenylephrine is an alpha-1 adrenergic receptor agonist. The chemical name of phenylephrine hydrochloride is (-)-m-hydroxy-α-[(methylamino) methyl] benzyl alcohol hydrochloride, its molecular formula is C9H13NO2· HCl (Molecular Weight: 203.67g/mol). Its structural formula is depicted below:

Phenylephrine hydrochloride is soluble in water and ethanol, and insoluble in chloroform and ethyl ether.

BIORPHEN Injection, 500 mcg/5 mL (100 mcg/mL):

BIORPHEN (phenylephrine hydrochloride) injection, 500 mcg/5 mL (100 mcg/mL),, is a sterile, nonpyrogenic, clear and colorless solution for intravenous use. It MUST NOT BE DILUTED before administration as an intravenous bolus.

Each mL contains: phenylephrine hydrochloride 100 mcg (equivalent to 80 mcg of phenylephrine base), sodium chloride 9.0 mg in water for injection. The pH is adjusted with hydrochloric acid if necessary. The pH range is 3.0 to 5.0.

BIORPHEN Injection, 10 mg/mL:

BIORPHEN (phenylephrine hydrochloride) injection, 10 mg/mL, is a sterile, nonpyrogenic, clear and colorless solution for intravenous use. It MUST BE DILUTED before administration as an intravenous bolus or continuous intravenous infusion.

Each mL contains: phenylephrine hydrochloride 10 mg (equivalent to 8.2 mg of phenylephrine base), sodium chloride 6.0 mg in water for injection. The pH is adjusted with hydrochloric acid if necessary. The pH range is 3.0 to 5.0.

12 CLINICAL PHARMACOLOGY

12.1 Mechanism of Action

Phenylephrine hydrochloride is an α-1 adrenergic receptor agonist.

12.2 Pharmacodynamics

Interaction of phenylephrine with α-1 adrenergic receptors on vascular smooth muscle cells causes activation of the cells and results in vasoconstriction. Following phenylephrine hydrochloride intravenous administration, increases in systolic and diastolic blood pressures, mean arterial blood pressure, and total peripheral vascular resistance are observed. The onset of blood pressure increase following an intravenous bolus phenylephrine hydrochloride administration is rapid, typically within minutes. As blood pressure increases following intravenous administration, vagal activity also increases, resulting in reflex bradycardia. Phenylephrine has activity on most vascular beds, including renal, pulmonary, and splanchnic arteries.

12.3 Pharmacokinetics

Following an intravenous infusion of phenylephrine hydrochloride, the observed effective half-life was approximately 5 minutes. The steady-state volume of distribution of approximately 340 L suggests a high distribution into organs and peripheral tissues. The average total serum clearance is approximately 2100 mL/min. The observed phenylephrine plasma terminal elimination half-life was 2.5 hours.

Phenylephrine is metabolized primarily by monoamine oxidase and sulfotransferase. After intravenous administration of radiolabeled phenylephrine, approximately 80% of the total dose was eliminated within first
12 h; and approximately 86% of the total dose was recovered in the urine within 48 h.

The excreted unchanged parent drug was 16% of the total dose in the urine at 48 h post intravenous administration. There are two major metabolites, with approximately 57 and 8% of the total dose excreted as m-hydroxymandelic acid and sulfate conjugates, respectively. The metabolites are considered not pharmacologically active.

13 NONCLINICAL TOXICOLOGY

13.1 Carcinogenesis, Mutagenesis, Impairment of Fertility

Carcinogenesis: Long-term animal studies that evaluated the carcinogenic potential of orally administered phenylephrine hydrochloride in F344/N rats and B6C3F1 mice were completed by the National Toxicology Program using the dietary route of administration. There was no evidence of carcinogenicity in mice administered approximately 270 mg/kg/day (131 times the human daily dose (HDD) of 10 mg/60 kg/day based on body surface area) or rats administered approximately 50 mg/kg/day (48 times the HDD).

Mutagenesis: Phenylephrine hydrochloride tested negative in the in vitro bacterial reverse mutation assay (S. typhimurium strains TA98, TA100, TA1535 and TA1537), the in vitro chromosomal aberrations assay, the in vitro sister chromatid exchange assay, and the in vivo rat micronucleus assay. Positive results were reported in only one of two replicates of the in vitro mouse lymphoma assay.

Impairment of Fertility: Phenylephrine did not impair mating, fertility, or reproductive outcome in normotensive male rats treated with 3 mg/kg/day phenylephrine via continuous intravenous infusion over 1 hour (2.9 times the HDD) for 28 days prior to mating and for a minimum of 63 days prior to sacrifice and female rats treated with the same dosing regimen for 14 days prior to mating and through Gestation Day 6. This dose was associated with increased mortality in both male and female rats and decreased body weight gain in treated males. There were decreased caudal sperm density and increased abnormal sperm reported in males treated with 3 mg/kg/day phenylephrine (2.9 times the HDD).

14 CLINICAL STUDIES

The evidence for the efficacy of BIORPHEN, is derived from studies of phenylephrine hydrochloride in the published literature. The literature support includes 16 studies evaluating the use of intravenous phenylephrine to treat hypotension during anesthesia. The 16 studies include 9 studies where phenylephrine was used in low-risk (ASA 1 and 2) pregnant women undergoing neuraxial anesthesia during Cesarean delivery, 6 studies in non-obstetric surgery under general anesthesia, and 1 study in non-obstetric surgery under combined general and neuraxial anesthesia. Phenylephrine has been shown to raise systolic and mean blood pressure when administered either as a bolus dose or by continuous infusion following the development of hypotension during anesthesia.

16 HOW SUPPLIED/STORAGE AND HANDLING

BIORPHEN (phenylephrine hydrochloride) injection is supplied as follows:

Unit of Sale | Strength | Each
NDC No. 43598-172-25; 5mL single-dose vial | 500 mcg/5mL; (100 mcg/mL) | NDC No. 43598-172-25; 5mL single-dose vial
NDC No. 43598-172-15 Pack of 10 single-dose ampules | 500 mcg/5mL; (100 mcg/mL) | NDC No. 43598-172-05 5 mL single-dose ampule
NDC No.43598-199-10 Pack of 10 single-dose ampules | 10 mg/mL | NDC No.43598-199-01 1 mL single-dose ampule

STORAGE AND HANDLING

Store BIORPHEN (phenylephrine hydrochloride) injection at 20°C to 25°C (68°F to 77°F), excursions permitted to 15°C to 30°C (59°F to 86°F) [see USP Controlled Room Temperature].

Discard any unused portion.

17 PATIENT COUNSELING INFORMATION

If applicable, inform patient, family member, or caregiver that certain medical conditions and medications might influence how BIORPHEN injection works.

Distributed by:
Dr. Reddy’s Laboratories Inc.,
Princeton, NJ 08540
Made in Switzerland

Issued: 04/2024

PACKAGE LABEL PRINCIPAL DISPLAY PANEL SECTION

PRINCIPAL DISPLAY PANEL - BIORPHEN (Phenylephrine Hydrochloride) Injection, USP 500 mcg/5 mL (100 mcg/mL) Ampule Label/Carton Label

500 mcg/5 mL (100 mcg/mL) Carton Label (10 single Dose Ampules per Carton)

PACKAGE LABEL PRINCIPAL DISPLAY PANEL SECTION

PRINCIPAL DISPLAY PANEL - BIORPHEN (Phenylephrine Hydrochloride) Injection, USP 500 mcg/5 mL (100 mcg/mL)Vial Label/Carton Label